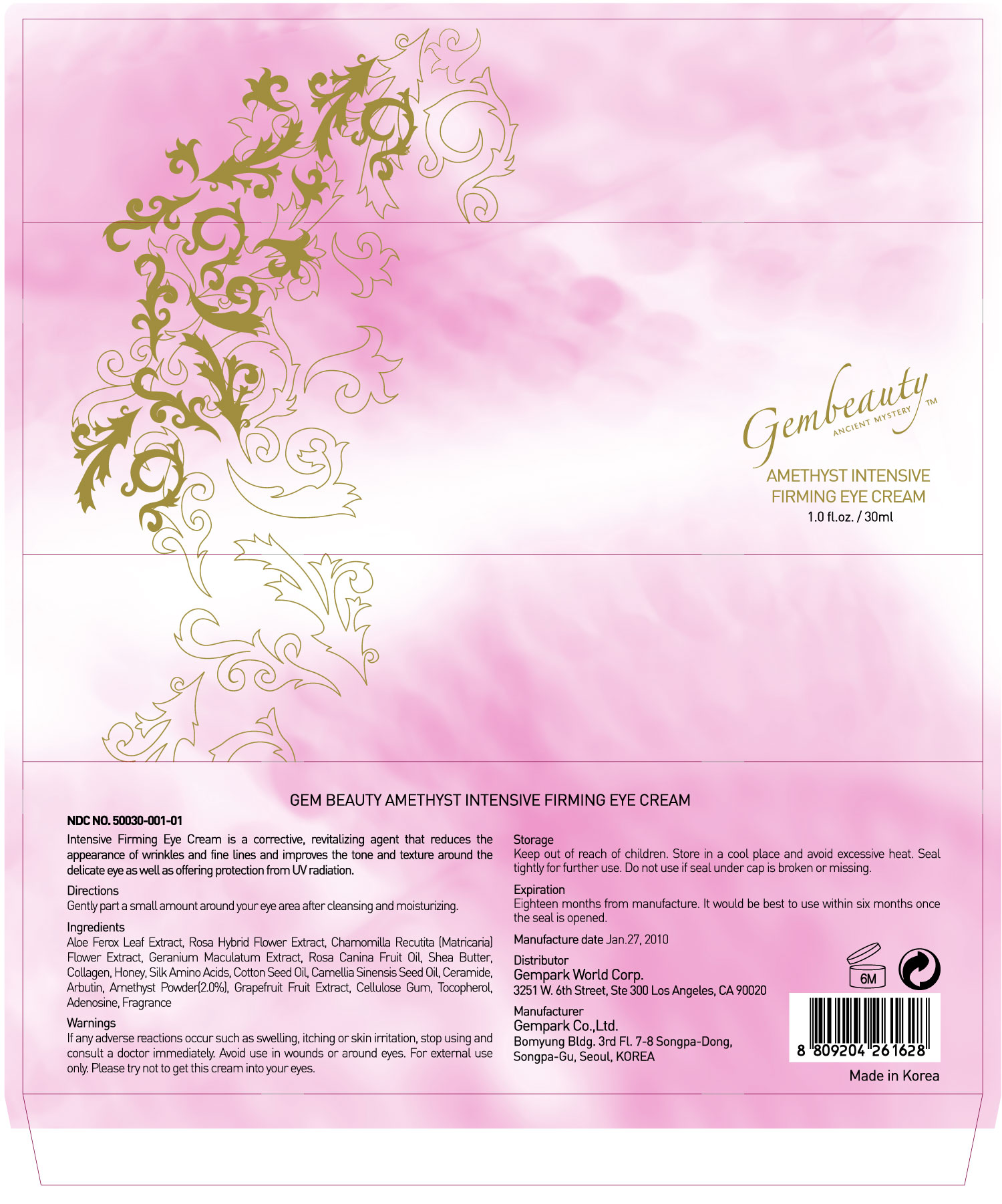 DRUG LABEL: GEM BEAUTY AMETHYST INTENSIVE FIRMING EYE CREAM
NDC: 50030-001 | Form: CREAM
Manufacturer: GEMPARK CO LTD
Category: otc | Type: HUMAN OTC DRUG LABEL
Date: 20091109

ACTIVE INGREDIENTS: ALOE VERA FLOWER 5.4 mL/30 mL

ACTIVE INGREDIENT

INGREDIENTS:

Aloe Ferox Leaf Extract, Rosa Hybrid Flower Extract, Chamomilla Recutitia [Matricaria] Flower Extract, Geranium Maculatum Extract, Rosa Canina Fruit Oil, Shea Butter, Collagen, Honey, Silk Amino Acids, Cotton Seed Oil, Carmellia Sinensis Seed Oil, Ceramide, Arbutin, Amethyst Powder, Grapefruit Fruit Extract, Cellulose Gum, Tocopherol, Adenosine, Fragrance

WARNINGS:

If any adverse reactions occur such as swelling, itching or skin irritation, stop using and consult a doctor immediately. Avoid use in wounds or around eyes. For external use only. Please try not to get this cream into your eyes.

DIRECTIONS:

Gently part a small amount around your eye area after cleansing and moisturizing.

STORAGE:

Keep out of reach of children. Store in a cool place and avoid excessive heat. Seal tightly for further use. Do not use if seal under cap is broken or missing.